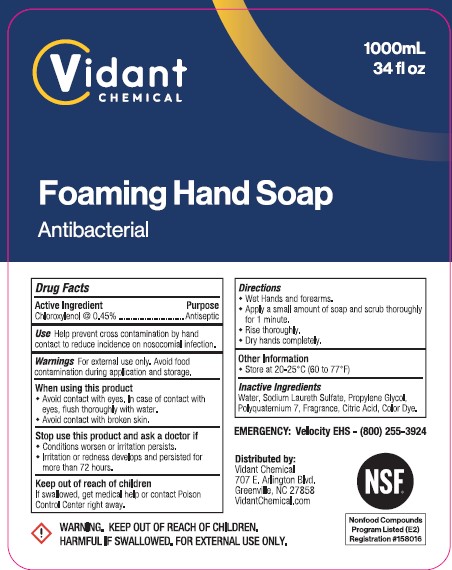 DRUG LABEL: FOAMING HAND

NDC: 83019-103 | Form: SOAP
Manufacturer: Draco Hygienic Products Inc.
Category: otc | Type: HUMAN OTC DRUG LABEL
Date: 20241008

ACTIVE INGREDIENTS: CHLOROXYLENOL 0.45 g/100 mL
INACTIVE INGREDIENTS: SODIUM LAURETH SULFATE; POLYQUATERNIUM-7 (70/30 ACRYLAMIDE/DADMAC; 1600 KD); ANHYDROUS CITRIC ACID; FD&C YELLOW NO. 5; WATER; PROPYLENE GLYCOL

Draco (as PLD) - VIDANT CHEMICAL - FOAMING HAND SOAP (83019-103)

ACTIVE INGREDIENT

CHLOROXYLENOL @ 0.45%

PURPOSE

ANTISEPTIC

USE

HELP PREVENT CROSS CONTAMINATION BY HAND CONTACT TO REDUCE INCIDENCE ON NOSOCOMIAL INFECTION.

WARNINGS

For external use only.

WHEN USING THIS PRODUCT

- AVOID CONTACT WITH EYES. IN CASE OF CONTACT WITH EYES, FLUSH THOROUGHLY WITH WATER.
- AVOID CONTACT WITH BROKEN SKIN.

STOP USE THIS PRODUCT AND ASK A DOCTOR IF

- CONDITIONS WORSEN OR IRRITATION PERSISTS.
- IRRITATION OR REDNESS DEVELOPS AND PERSISTED FOR MORE THAN 72 HOURS.

Keep out of reach of children
lf swallowed,get medical help or contact Poison Control Center right away.

DIRECTIONS

- WET HANDS AND FOREARMS.
- APPLY A SMALL AMOUNT OF SOAP AND SCRUB THOROUGHLY FOR 1 MINUTE.
- RINSE THOROUGHLY.
- DRY HANDS COMPLETELY.

OTHER INFORMATION

- Store below 20-25°C (60 TO 77°F)

INACTIVE INGREDIENTS

Water, Sodium Laureth Sulfate, Propylene Glycol, Polyquaternium 7, Fragrance, Citric Acid, Color Dye.